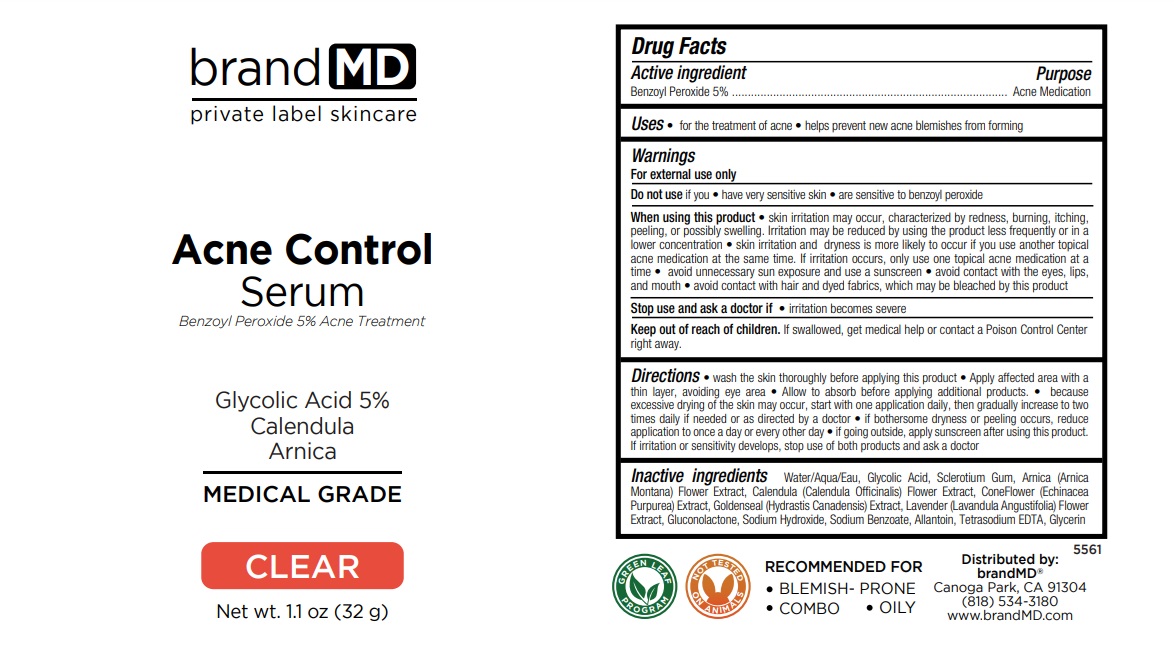 DRUG LABEL: Acne Control Serum
NDC: 72957-001 | Form: LOTION
Manufacturer: Private Label Skin Care
Category: otc | Type: HUMAN OTC DRUG LABEL
Date: 20250226

ACTIVE INGREDIENTS: BENZOYL PEROXIDE 5 g/100 g
INACTIVE INGREDIENTS: WATER; GLYCOLIC ACID; BETASIZOFIRAN; ARNICA MONTANA FLOWER; CALENDULA OFFICINALIS FLOWER; ECHINACEA PURPUREA WHOLE; GOLDENSEAL; LAVANDULA ANGUSTIFOLIA SUBSP. ANGUSTIFOLIA FLOWER; GLUCONOLACTONE; SODIUM HYDROXIDE; SODIUM BENZOATE; ALLANTOIN; EDETATE SODIUM; GLYCERIN

Acne Control Serum

Active ingredient

Benzoyl Peroxide 5%

Purpose

Acne Medication

Uses

• for the treatment of acne • helps prevent new acne blemishes from forming

Warnings

For external use only

Do not use if you • have very sensitive skin • are sensitive to benzoyl peroxide

When using this product • skin irritation may occur, characterized by redness, burning, itching, peeling, or possibly swelling. Irritation may be reduced by using the product less frequently or in a lower concentration • skin irritation and dryness is more likely to occur if you use another topical acne medication at the same time. If irritation occurs, only use one topical acne medication at a time • avoid unnecessary sun exposure and use a sunscreen • avoid contact with the eyes, lips, and mouth • avoid contact with hair and dyed fabrics, which may be bleached by this product

Stop use and ask a doctor if • irritation becomes severe

Keep out of reach of children. If swallowed, get medical help or contact a Poison Control Center right away.

Directions

• wash the skin thoroughly before applying this product • Apply affected area with a thin layer, avoiding eye area • Allow to absorb before applying additional products. • because excessive drying of the skin may occur, start with one application daily, then gradually increase to two times daily if needed or as directed by a doctor • if bothersome dryness or peeling occurs, reduce application to once a day or every other day • if going outside, apply sunscreen after using this product. If irritation or sensitivity develops, stop use of both products and ask a doctor

Inactive ingredients

Water/Aqua/Eau, Glycolic Acid, Sclerotium Gum, Arnica (Arnica Montana) Flower Extract, Calendula (Calendula Officinalis) Flower Extract, ConeFlower (Echinacea Purpurea) Extract, Goldenseal (Hydrastis Canadensis) Extract, Lavender (Lavandula Angustifolia) Flower Extract, Gluconolactone, Sodium Hydroxide, Sodium Benzoate, Allantoin, Tetrasodium EDTA, Glycerin

brand MD

Benzoyl Peroxide 5% Acne Treatment

Glycolic Acid 5%
Calendula
Arnica

MEDICAL GRADE

CLEAR

RECOMMENDED FOR
• BLEMISH- PRONE
• COMBO • OILY

GREEN LEAF PROGRAM

NOT TESTED ON ANIMALS

Distributed by:
brandMD®
Canoga Park, CA 91304
(818) 534-3180
www.brandMD.com